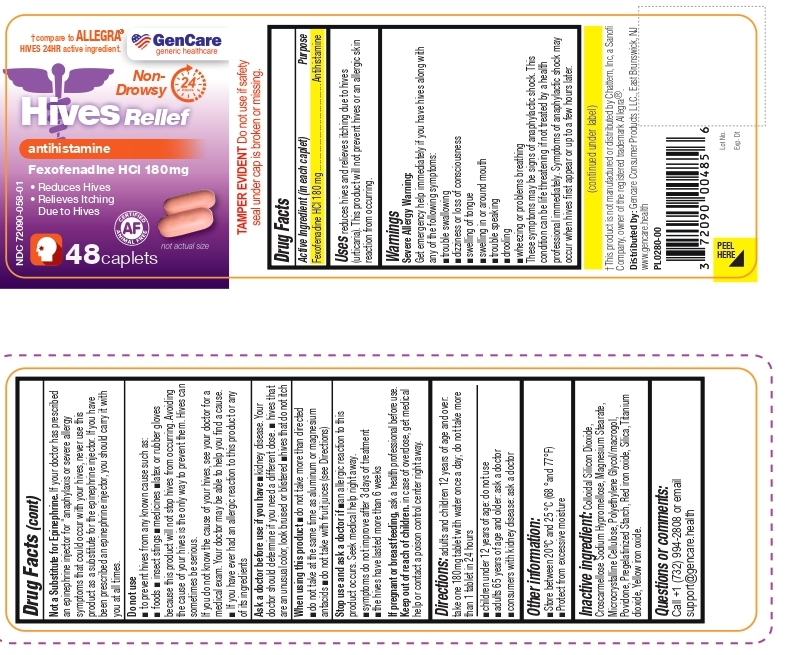 DRUG LABEL: Gencare Hives Relief
NDC: 72090-058 | Form: TABLET
Manufacturer: Pioneer Life Sciences, LLC
Category: otc | Type: HUMAN OTC DRUG LABEL
Date: 20260121

ACTIVE INGREDIENTS: FEXOFENADINE HYDROCHLORIDE 180 mg/1 1
INACTIVE INGREDIENTS: SILICON DIOXIDE; CROSCARMELLOSE SODIUM; HYPROMELLOSE, UNSPECIFIED; MAGNESIUM STEARATE; MICROCRYSTALLINE CELLULOSE; POLYETHYLENE GLYCOL, UNSPECIFIED; POVIDONE, UNSPECIFIED; STARCH, CORN; FERRIC OXIDE RED; TITANIUM DIOXIDE; FERRIC OXIDE YELLOW

Gencare Hives Relief

Active Ingredient (in each caplet)

Fexofenadine HCl 180 mg

Purpose

Antihistamine

Uses

reduces hives and relieves itching due to hives (urticaria). This product will not prevent hives or an allergic skin reaction from occurring.

Warnings

Severe Allergy Warning:
Get emergency help immediately if you have hives along with any of the following symptoms:
■trouble swallowing
■dizziness or loss of consciousness
■swelling of tongue
■swelling in or around mouth
■trouble speaking
■drooling
■wheezing or problems breathing

These symptoms may be signs of anaphylactic shock. This condition can be life threatening if not treated by a health professional immediately. Symptoms of anaphylactic shock may occur when hives first appear or up to a few hours later.

Not a Substitute for Epinephrine. If your doctor has prescribed an epinephrine injector for "anaphylaxis or severe allergy symptoms that could occur with your hives, never use this product as a substitute for the epinephrine injector. If you have been prescribed an epinephrine injector, you should carry it with you at all times.

Do not use

■ to prevent hives from any known cause such as:
■ foods ■ insect stings ■medicines ■latex or rubber gloves because this product will not stop hives from occurring. Avoiding the cause of your hives is the only way to prevent them. Hives can sometimes be serious.
If you do not know the cause of your hives, see your doctor for a medical exam. Your doctor may be able to help you find a cause.
■ If you have ever had an allergic reaction to this product or any of its ingredients

Ask a doctor before use if you have

■ kidney disease. Your doctor should determine if you need a different dose. ■ hives that are an unusual color, look bruised or blistered ■hives that do not itch

When using this product

■do not take more than directed
■do not take at the same time as aluminum or magnesium antacids

■do not take with fruit juices (see Directions)

Stop use and ask a doctor if

■ an allergic reaction to this product occurs. Seek medical help right away.
■ symptoms do not improve after 3 days of treatment
■ the hives have lasted more than 6 weeks

PREGNANCY OR BREAST FEEDING

If pregnant or breast feeding, ask a health professional before use.

Keep out of reach of children. in case of overdose, get medical help or contact a poison control center right away.

Directions

adults and children 12 years of age and over: take one 180mg tablet with water once a day; do not take more than 1 tablet in 24 hours

■children under 12 years of age: do not use
■adults 65 years of age and older: ask a doctor
■consumers with kidney disease: ask a doctor

Other information

■ Store between 20°C and 25 °C (68 °and 77°F)
■ Protect from excessive moisture

Inactive ingredient

Colloidal Silicon Dioxide, Croscarmellose Sodium Hypromellose, Magnesium Stearate, Microcrystalline Cellulose, Polyethylene Glycol/macrogol, Povidone, Pregelatinized Starch, Red iron oxide, Silica, Titanium dioxide, Yellow iron oxide.

Questions or comments

Call +1 (732) 994-2808 or email support@gencare.health